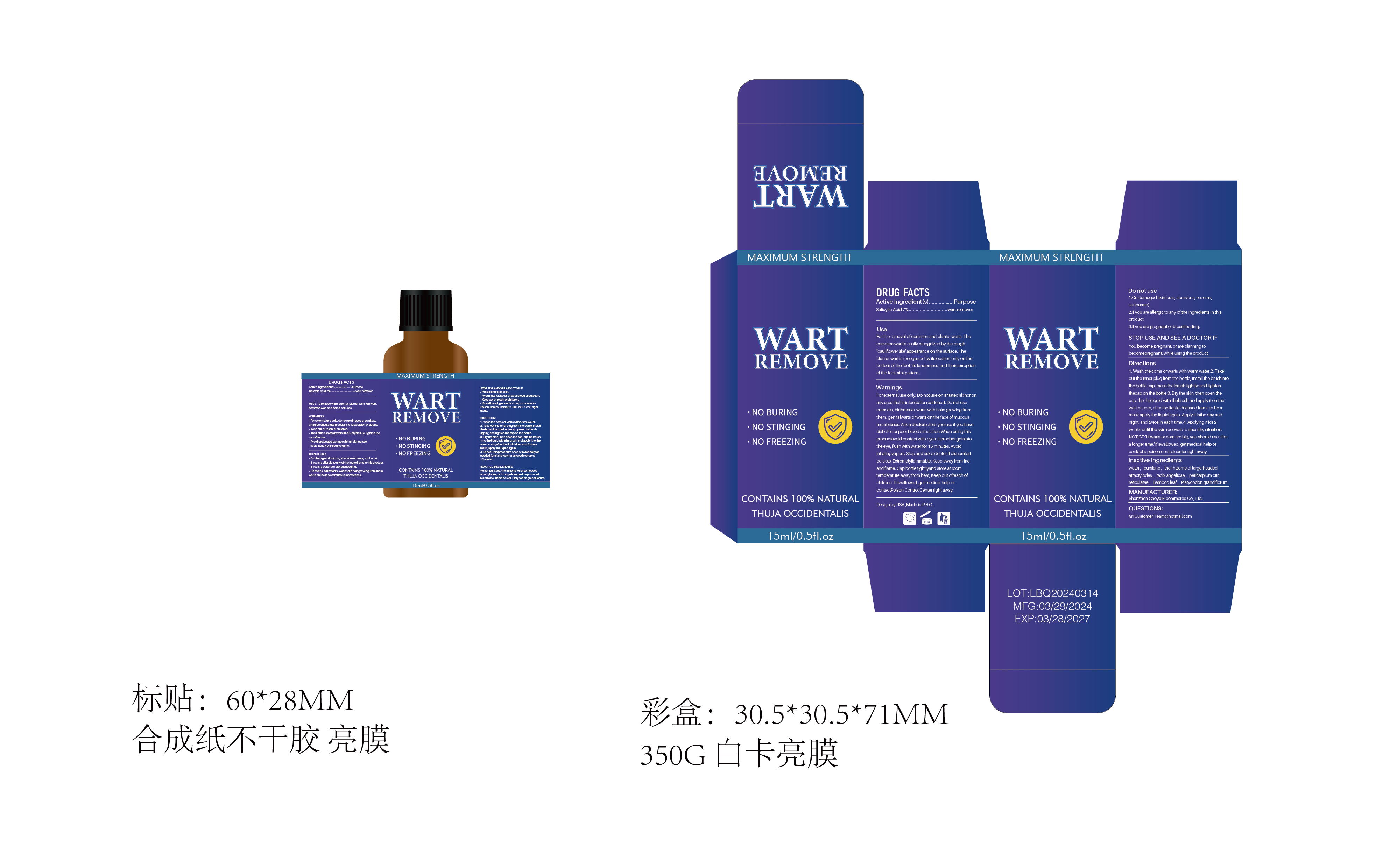 DRUG LABEL: WART REMOVE
NDC: 84322-001 | Form: LIQUID
Manufacturer: Shenzhen Gaoye E-commerce Co., Ltd
Category: otc | Type: HUMAN OTC DRUG LABEL
Date: 20240515

ACTIVE INGREDIENTS: SALICYLIC ACID 7 g/100 mL
INACTIVE INGREDIENTS: ANGELICA DAHURICA VAR. FORMOSANA WHOLE; PURSLANE; BAMBUSA VULGARIS LEAF; WATER; TANGERETIN

84322-001

Active Ingredient(s)

salicylic acid-7%

Purpose

wart remover

Use

For the removal of common and plantar warts. The common wart s esly lecogntzed by the rough
'Cau iflower like'appearance on the surface. The plantarwart is reoognized by tslocationo only on the
bottomof the foot, its tenderness and theinteruption of the footpint pattern.

Warnings

For extemal use only. DO not use on iritated skinor on any area that is infected or reddened. Do notuse
onmoles, birthmarks, warts with hairs growing from them, genitalwarts or warts on the face of mucous
membranes Ask a doctorbefore youuse if youhave diabetes or poor blood circulatin.Whenusing this
productavoid contact with eyes. f product getsinto the eye, flushwith water for 15 minutes. Avold
inhalingvapors. Stop and ask a doctor if discomfort persists. Extremelyflammable. Keep away from fre
and flame. Cap botte tghtyand store at room temperature away from heat Keep out ofreachof
children. If swallowed, get medicalhelp or contactPoison Control Center right away.

Do not use

1.On damaged skin(cuts, abrasions, eczema, sunburmn).
2.If you are llergie to any of the ingredients in this product
3.f you are pregnant or besteeding.

When using this product keep out of eyes, ears, and mouth. In case of contact with eyes, rinse eyes thoroughly with water.

STOP USE

●if discomfort persists.
●if you have diabetes or poor blood circulation.
●Keep out of reach of children.
●If swallowed, get medical help or contact a Poison Control Center (1-800-222-1222) right away.

Keep out of reach of children. If swallowed, get medical help or contact a Poison Control Center right away.

Directions

1. Wash the corns or warts with warm water.
2. Take out the inner plug from the bottle, install the brush into the bottle cap. press the brush
tightly, and tighten the cap on the bottle.
3. Dry the skin, then open the cap, dip the brush into the liquid with the brush and apply it to
the wart or corn,after the liquid dries and forms a mask, apply the liquid again.
4. Repeat this procedure once or twice daily as needed (until the wart is removed) for up
to 12 weeks.

Other information

No data available

Inactive ingredients

Water, purslane, the rhizome of largeheaded atractylodes, radix angelicae, pericarpium citri
reticulatae, Bamboo leaf, Platycodon grandiflorum.